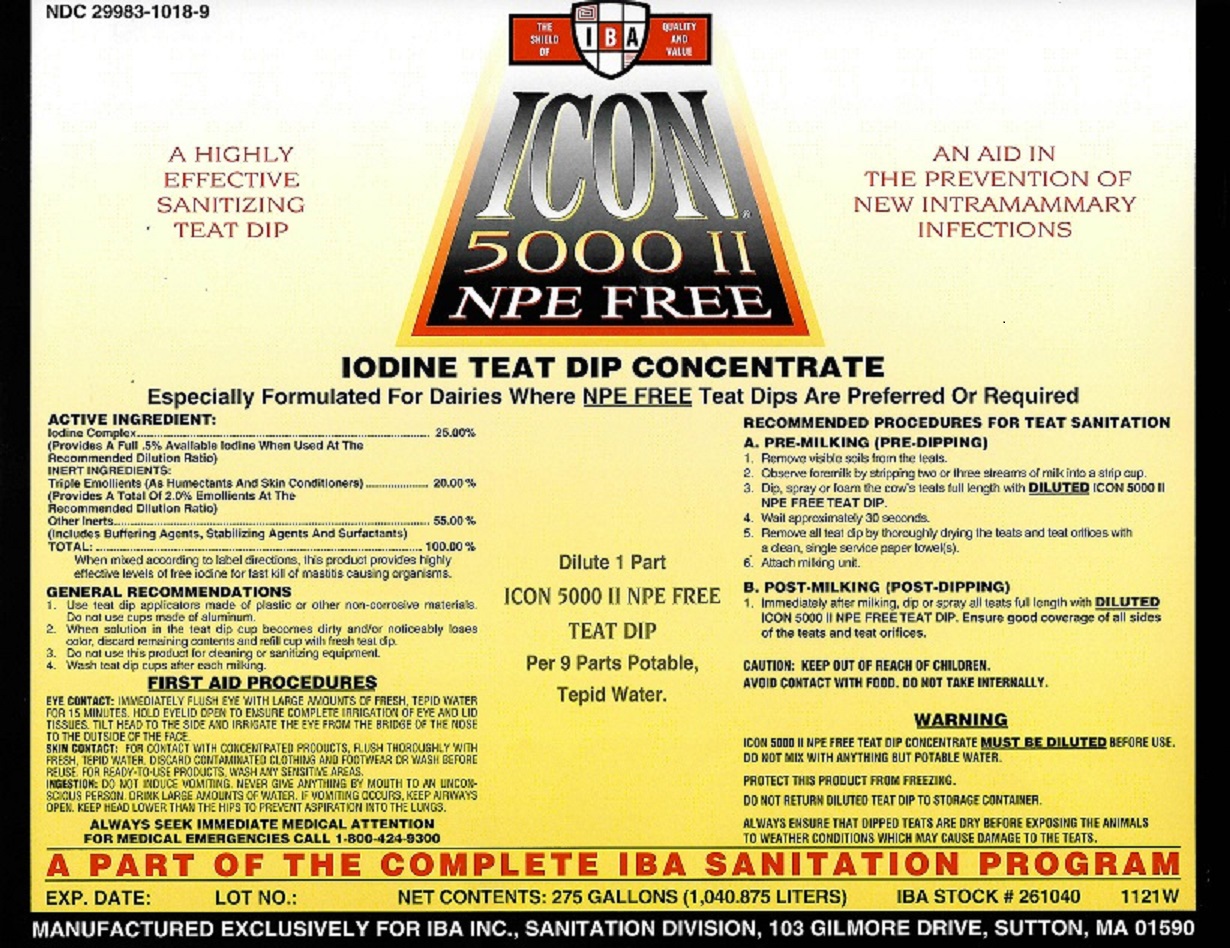 DRUG LABEL: ICON 5000 II
NDC: 29983-1018 | Form: LIQUID
Manufacturer: IBA
Category: animal | Type: OTC ANIMAL DRUG LABEL
Date: 20251202

ACTIVE INGREDIENTS: IODINE 0.5 kg/100 kg

ICON 5000 II - NPE FREE

ACTIVE INGREDIENTS:

Iodine Complex:...........................................25.00%

(Provide a full .5% available iodine when used at the recommended dilution ratio)

INERT INGREDIENTS:

Triple Emollient Syste (As Humectants And Skin Conditioners):..........................................20.00%

(Provides a total of 2.0% emollients at the recommended dilution ratio)

Other Inerts................................................................................................................55.00%

(Includes Buffering Agents, Stabilizing Agents, And Surfactants)

TOTAL:.......................................................................................................................100.00%

GENERAL RECOMMENDATIONS

1. Use teat dip applicators made of plastic or other non-corrosive materials. Do not use cups made of aluminum.

2. When soluiton in the teat dip cup becomes dirty and/or noticebly loses color. discard remaining contents and refill cup with fresh teat dip.

3. Do not use this product for cleaning or sanitizing equipment.

4. Wash teat dip cups after each milking.

CAUTION

KEEP OUT OF REACH OF CHILDREN. AVOID CONTACT WITH FOOD. DO NOT TAKE INTERNALLY.

FIRST AID

FIRST AID: IF TAKEN INTERNALLY, DRINK LARGE QUANTITIES OF WATER AND GET IMMEDIATE MEDICAL ATTENTION. IN CASE OF CONTACT WITH EYES, FLUSH LIBERALLY WITH TEPID WATER AND GET MEDICAL ATTENTION. NEVER GIVE ANYHTING BY MOUTH TO AN UNCONSCIOUS PERSON.

FOR MEDICAL EMERGENCIES CALL 1-303-623-5716

RECOMMENDED PROCEDURES FOR TEAT SANITATION

A. PRE-MILKING (PRE-DIPPING)

1. Remove visible soils from the teats.

2. Onserve foremilk by stripping two or three streams of milk into a strip cup.

3. Dip or spray teh cow's teats full length with diluted ICON 5000 II Teat Dip.

4. Wait approximately 30 seconds.

5. Remove all teat dip by thoroughly drying the teats and teat orifices with a clean, single service paper towel(s).

6. Attach milking unit

B.POST -MILKING (POST-DIPPING)

1. Immediately after milking, dip or spray all teats full length with diluted ICON 5000 II Teat Dip. Ensure good coverage of all sides of the teats and teat orifices.

Dilute 1 part ICON 5000 II TEAT DIP per 9 parts potable , tepid water.

WARNING

WARNING: ICON 5000 II TEAT DIP CONCENTRATE MUST BE DILUTED BEFORE USE. DO NOT MIX WITH ANYTHING BUT POTABLE WATER. DO NOT RETURN TEAT DIP LEFT IN THE TEAT DIPPER TO STORAGE CONTAINER. ENSURE THAT DIPPED TEATS ARE DRY BEFORE EXPOSING THE ANIMALS TO WEATHER CONDITIONS WHICH MAY CAUSE DAMGE TO THE TEATS.